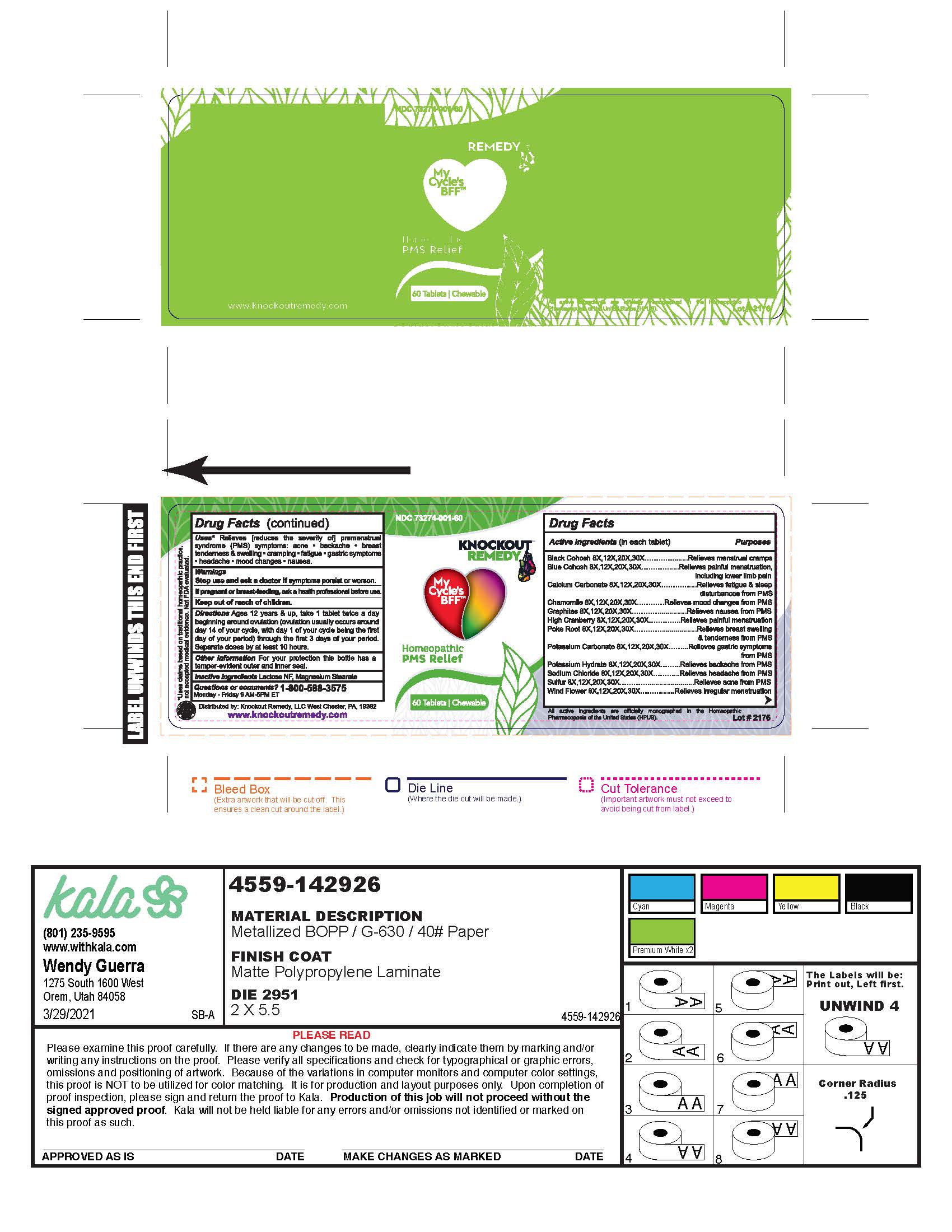 DRUG LABEL: My Cycles BFF
NDC: 73274-001 | Form: TABLET, CHEWABLE
Manufacturer: Knockout Remedy, LLC
Category: homeopathic | Type: HUMAN OTC DRUG LABEL
Date: 20210518

ACTIVE INGREDIENTS: VIBURNUM OPULUS ROOT 30 [hp_X]/1 1; CAULOPHYLLUM THALICTROIDES ROOT 30 [hp_X]/1 1; PULSATILLA VULGARIS 30 [hp_X]/1 1; PHYTOLACCA AMERICANA ROOT 30 [hp_X]/1 1; POTASSIUM HYDROXIDE 30 [hp_X]/1 1; POTASSIUM CARBONATE 30 [hp_X]/1 1; SULFUR 30 [hp_X]/1 1; BLACK COHOSH 30 [hp_X]/1 1; SODIUM CHLORIDE 30 [hp_X]/1 1; CHAMOMILE 30 [hp_X]/1 1; CALCIUM CARBONATE 30 [hp_X]/1 1; GRAPHITE 30 [hp_X]/1 1
INACTIVE INGREDIENTS: LACTOSE MONOHYDRATE; MAGNESIUM STEARATE

My Cycle's BFF

Drug Facts

Active Ingredients | Purpose
Black Cohosh 8X, 12X, 20X, 30X | Relieves menstrual cramps
Blue Cohosh 8X, 12X, 20X, 30X | Relieves painful menstruation, including lower limb pain
Calcium Carbonate 8X, 12X, 20X, 30X | Relieves fatigue & sleep disturbances from PMS
Chamomile 8X, 12X, 20X, 30X | Relieves mood changes from PMS
Graphites 8X, 12X, 20X, 30X | Relieves nausea from PMS
High Cranberry 8X, 12X, 20X, 30X | Relieves painful mensturation
Poke Root 8X, 12X, 20X, 30X | Relieves breast swelling & tenderness from PMS
Potassium Carbonate 8X, 12X, 20X, 30X | Relieves gastic symptoms from PMS
Potassium Hydrate 8X, 12X, 20X, 30X | Relieves backache from PMS
Sodium Chloride 8X, 12X, 20X, 30X | Relieves headache from PMS
Sulfur 8X, 12X, 20X, 30X | Relieves acne from PMS
Wind Flower 8X, 12X, 20X, 30X | Relieves irregular menstruation

Uses

Relieves [reduces the severity of] premenstrual syndrome (PMS) symptoms: acne, backache, breast tenderness & swelling, cramping, fatigue, gastic symptoms, headache, mood changes, nausea

Purpose

Homeopathic PMS Relief

Warnings

Stop use and ask a doctor is symptoms persist or worsen.

If pregnant or breast-feeding, ask a health professional before use.

Keep out of reach of children.

Directions

Ages 12 years & up, take 1 tablet twice a day beginning around ovulation (ovulation usually occurs around day 14 of your cycle, with day 1 of your cycle being the first day of your period) through the first 3 days of your period. Seperate doses by at least 10 hours.

Other information

For your protection this bottle has a tamper-evident outer and inner seal.

Inactive Ingredients

Lactose NF, Magnesium Stearate